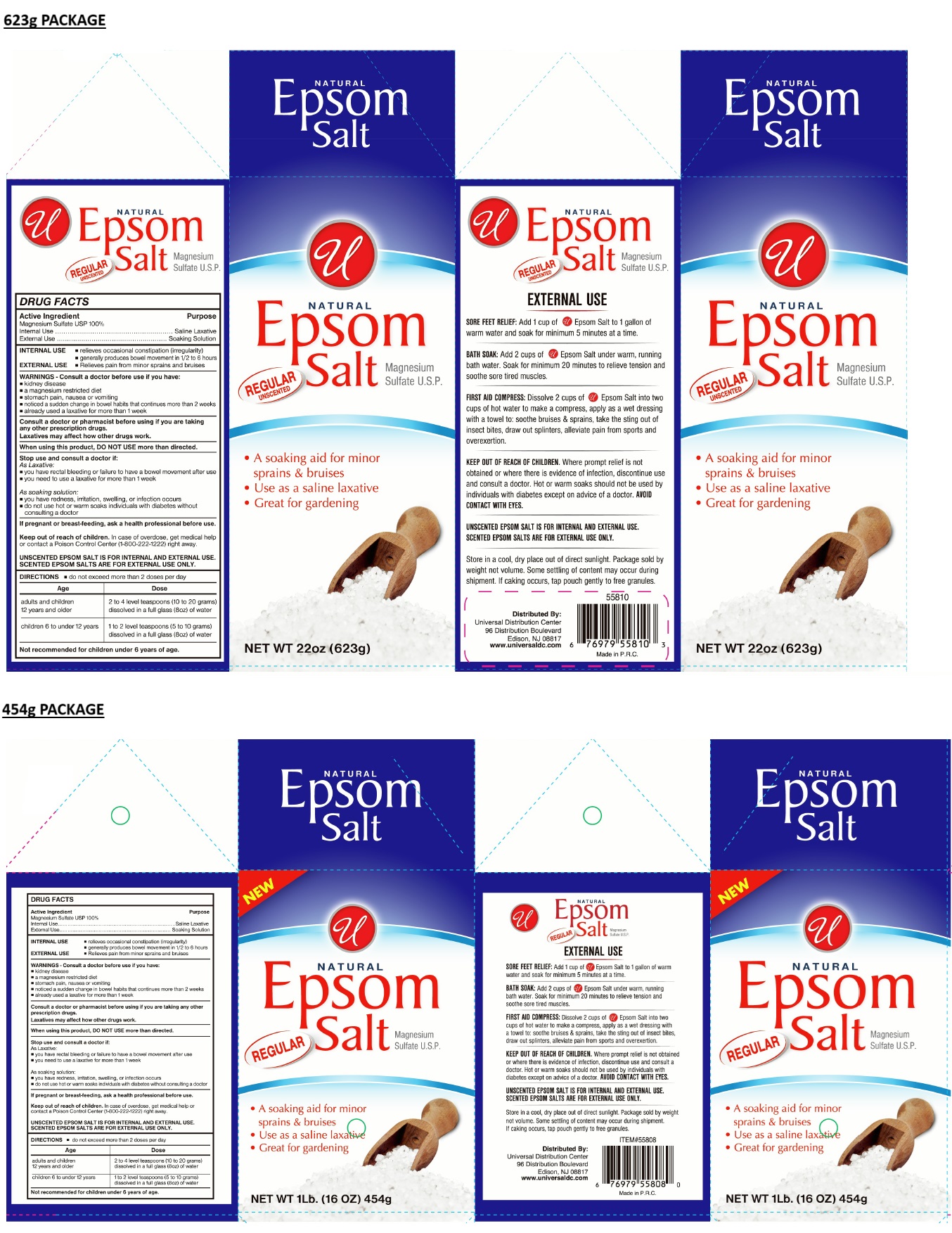 DRUG LABEL: NATURAL Epsom Salt
NDC: 52000-420 | Form: GRANULE
Manufacturer: Universal Distribution Center LLC
Category: otc | Type: HUMAN OTC DRUG LABEL
Date: 20241016

ACTIVE INGREDIENTS: MAGNESIUM SULFATE, UNSPECIFIED FORM 100 g/100 g

NATURAL Epsom Salt

Active Ingredient

Magnesium Sulfate USP 100%

Purpose

Internal Use.............................................Saline Laxative

External Use...........................................Soaking Solution

INDICATIONS AND USAGE

INTERNAL USE
• relieves occasional constipation (irregularity)
• generally produces bowel movement in 1/2 to 6 hours

EXTERNAL USE
• Relieves pain from minor sprains and bruises

WARNINGS

WARNINGS - Consult a doctor before use if you have:
• kidney disease
• a magnesium restricted diet
• stomach pain, nausea or vomiting
• noticed a sudden change in bowel habits that continues more than 2 weeks
• already used a laxative for more than 1 week

Consult a doctor or pharmacist before using if you are taking any other prescription drugs.

Laxatives may affect how other drugs work.

When using this product, DO NOT USE more than directed.

Stop use and consult a doctor if:
As Laxative:
• you have rectal bleeding or failure to have a bowel movement after use
• you need to use a laxative for more than 1 week

As soaking solution:
• you have redness, irritation, swelling, or infection occurs
• do not use hot or warm soaks individuals with diabetes without consulting a doctor

If pregnant or breast-feeding, ask a health professional before use.

Keep out of reach of children. In case of overdose, get medical help or contact a Poison Control Center (1-800-222-1222) right away.

UNSCENTED EPSOM SALT IS FOR INTERNAL AND EXTERNAL USE. SCENTED EPSOM SALTS ARE FOR EXTERNAL USE ONLY.

DIRECTIONS

• do not exceed more than 2 doses per day

Age | Dose
adults and children 12 years and older | 2 to 4 level teaspoons(10 to 20 grams) dissolved in a full glass (8oz) of water
children 6 to under 12 years | 1 to 2 level teaspoons(5 to 10 grams) dissolved in a full glass (8oz) of water

Not recommended for children under 6 years of age.

INACTIVE INGREDIENT

None

REGULAR UNSCENTED

• A soaking aid for minor sprains & bruises

• Use as a saline laxative

• Great for gardening

EXTERNAL USE

SORE FEET RELIEF: Add 1 cup of Epsom Salt to 1 gallon of warm water and soak for minimum 5 minutes at a time.

BATH SOAK: Add 2 cups of Epsom Salt under warm, running bath water. Soak for minimum 20 minutes to relieve tension and soothe sore tired muscles.

FIRST AID COMPRESS: Dissolve 2 cups of Epsom Salt into two cups of hot water to make a compress, apply as a wet dressing with a towel to: soothe bruises & sprains, take the sting out of insect bites, draw out splinters, alleviate pain from sports and overexertion.

KEEP OUT OF REACH OF CHILDREN. Where prompt relief is not obtained or where there is evidence of infection, discontinue use and consult a doctor. Hot or warm soaks should not be used by individuals with diabetes except on advice of a doctor. AVOID CONTACT WITH EYES.

Store in a cool, dry place out of direct sunlight. Package sold by weight not volume. Some settling of content may occur during shipment. If caking occurs, tap pouch gently to free granules.

Distributed By:
Universal Distribution Center
96 Distribution Boulevard
Edison, NJ 08817
www.universaldc.com